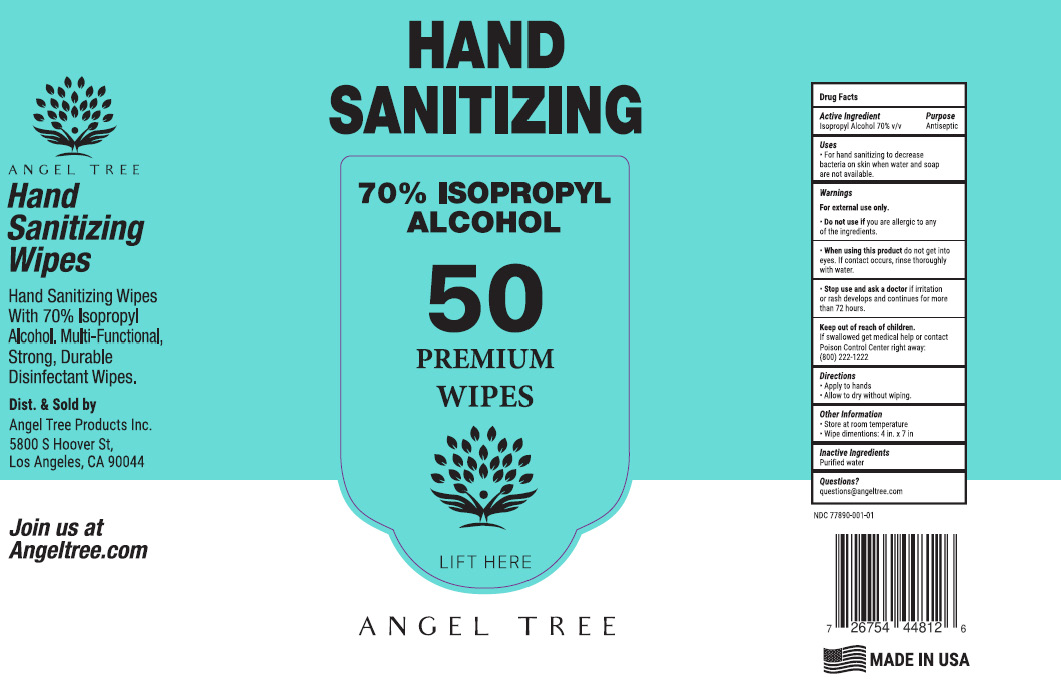 DRUG LABEL: Hand Sanitizing Wipes
NDC: 77890-001 | Form: CLOTH
Manufacturer: Angel Tree Products Inc.
Category: otc | Type: HUMAN OTC DRUG LABEL
Date: 20200701

ACTIVE INGREDIENTS: ISOPROPYL ALCOHOL 70 1/100 1
INACTIVE INGREDIENTS: WATER

Active Ingredient(s)

Isopropyl Alcohol 70% v/v. Purpose: Antiseptic

Purpose

Antiseptic

Use

- For hand sanitizing to decrease bacteria on skin when water and soap are not available.

Warnings

For external use only.

Do not use

if you are allergic to any of the ingredients.

When using this product do not get into eyes. If contact occurs, rinse eyes thoroughly with water.

Stop use and ask a doctor if irritation or rash develops and continues for more than 72 hours.

Keep out of reach of children. If swallowed, get medical help or contact a Poison Control Center right away: (800) 222-1222

Directions

- Apply to hands
- Allow to dry without wiping.

Other information

- Store at room temperature
- Wipe dimensions: 4 in x 7 in

Inactive ingredients

Purified water

Questions?

questions@angeltree.com

Package Label - Principal Display Panel

50 Wipes NDC: 77890-001-01